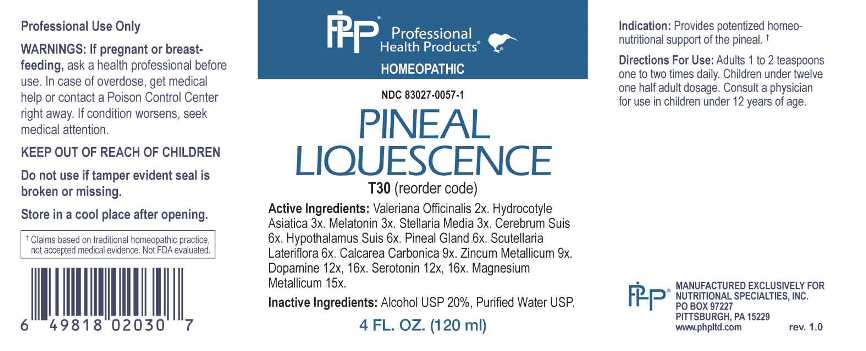 DRUG LABEL: Pineal Liquescence
NDC: 83027-0057 | Form: LIQUID
Manufacturer: Nutritional Specialties, Inc.
Category: homeopathic | Type: HUMAN OTC DRUG LABEL
Date: 20240724

ACTIVE INGREDIENTS: VALERIAN 2 [hp_X]/1 mL; CENTELLA ASIATICA WHOLE 3 [hp_X]/1 mL; MELATONIN 3 [hp_X]/1 mL; STELLARIA MEDIA 3 [hp_X]/1 mL; SUS SCROFA CEREBRUM 6 [hp_X]/1 mL; SUS SCROFA PITUITARY GLAND 6 [hp_X]/1 mL; SUS SCROFA PINEAL GLAND 6 [hp_X]/1 mL; SCUTELLARIA LATERIFLORA WHOLE 6 [hp_X]/1 mL; OYSTER SHELL CALCIUM CARBONATE, CRUDE 9 [hp_X]/1 mL; ZINC 9 [hp_X]/1 mL; DOPAMINE HYDROCHLORIDE 12 [hp_X]/1 mL; SEROTONIN HYDROCHLORIDE 12 [hp_X]/1 mL; MAGNESIUM 15 [hp_X]/1 mL
INACTIVE INGREDIENTS: WATER; ALCOHOL

DRUG FACTS:

ACTIVE INGREDIENTS:

Valeriana Officinalis 2X, Hydrocotyle Asiatica 3X, Melatonin 3X, Stellaria Media 3X, Cerebrum Suis 6X, Hypothalamus Suis 6x, Pineal Gland 6X, Scutellaria Lateriflora 6X, Calcarea Carbonica 9X, Zincum Metallicum 9X, Dopamine 12X, 16X, Serotonin 12X, 16X, Magnesium Metallicum 15X.

PURPOSE:

Provides potentized homeo-nutritional support of the pineal.†

†Claims based on traditional homeopathic practice, not accepted medical evidence. Not FDA evaluated.

WARNINGS:

Professional Use Only

If pregnant or breast-feeding, ask a health professional before use.

In case of overdose, get medical help or contact a Poison Control Center right away.

If condition worsens, seek medical attention.

KEEP OUT OF REACH OF CHILDREN

Do not use if tamper evident seal is broken or missing.

Store in a cool place after opening

KEEP OUT OF REACH OF CHILDREN:

In case of overdose, get medical help or contact a Poison Control Center right away.

DIRECTIONS:

Adults 1 to 2 teaspoons one to two times daily. Children under twelve one half adult dosage. Consult a physician for use in children under 12 years of age.

INDICATIONS:

Provides potentized homeo-nutritional support of the pineal.†

†Claims based on traditional homeopathic practice, not accepted medical evidence. Not FDA evaluated.

INACTIVE INGREDIENTS:

Alcohol USP 20%, Purified Water USP.

QUESTIONS:

MANUFACTURED EXCLUSIVELY FOR

NUTRITIONAL SPECIALTIES, INC.

PO BOX 97227

PITTSBURG, PA 15229

www.phpltd.com

PACKAGE LABEL DISPLAY:

Professional

Health Products

HOMEOPATHIC

NDC 83027-0057-1

PINEAL

LIQUESCENCE

4 FL. OZ (120 ml)